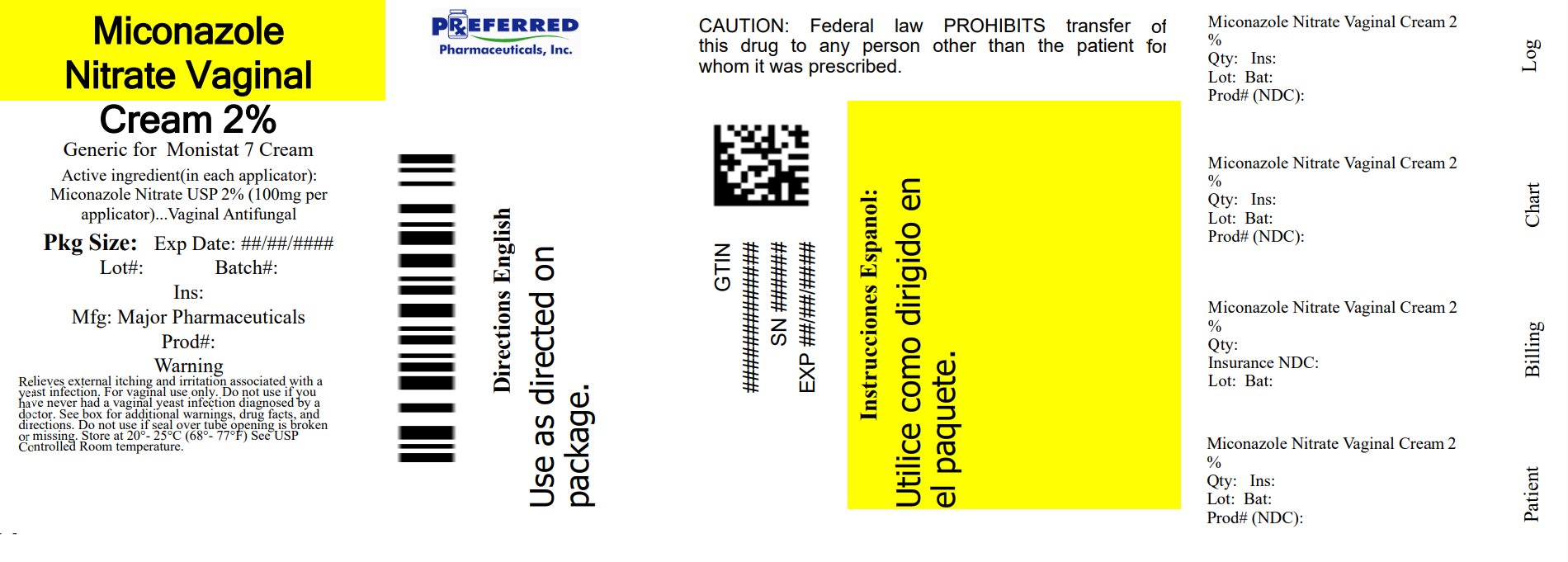 DRUG LABEL: Miconazole 7
NDC: 68788-8661 | Form: CREAM
Manufacturer: Preferred Pharmaceuticals Inc.
Category: otc | Type: HUMAN OTC DRUG LABEL
Date: 20250812

ACTIVE INGREDIENTS: MICONAZOLE NITRATE 20 mg/1 g
INACTIVE INGREDIENTS: BENZOIC ACID; BUTYLATED HYDROXYANISOLE; MINERAL OIL; APRICOT KERNEL OIL PEG-6 ESTERS; PEGOXOL 7 STEARATE; WATER

Miconazole Nitrate Vaginal Cream, USP

Active ingredient

Miconazole nitrate, USP 2% (100 mg in each applicator)

Purpose

Vaginal antifungal

Uses

- treats vaginal yeast infections
- relieves external itching and irritation due to a vaginal yeast infection

Warnings

For vaginal use only

Do not use

if you have never had a vaginal yeast infection diagnosed by a doctor

Ask a doctor before use if you have

- vaginal itching and discomfort for the first time
- lower abdominal, back, or shoulder pain, fever, chills, nausea, vomiting, or foul-smelling vaginal discharge. You may have a more serious condition.
- vaginal yeast infections often (such as once a month or 3 in 6 months). You could be pregnant or have a serious underlying medical cause for your symptoms, including diabetes or a weakened immune system.
- been exposed to the human immunodeficiency virus (HIV) that causes AIDS

Ask a doctor or pharmacist before use if you are

taking the prescription blood thinning medicine warfarin, because bleeding or bruising may occur

When using this product

- do not use tampons, douches, spermicides or other vaginal products. Condoms and diaphragms may be damaged and fail to prevent pregnancy or sexually transmitted diseases (STDs).
- do not have vaginal intercourse
- mild increase in vaginal burning, itching or irritation may occur
- if you do not get complete relief ask a doctor before using another product.

Stop use and ask a doctor if

- symptoms do not get better in 3 days
- symptoms last more than 7 days
- you get a rash or hives, abdominal pain, fever, chills, nausea, vomiting, or foul-smelling vaginal discharge

If pregnant or breast-feeding,

ask a health professional before use.

Keep out of reach of children.

If swallowed, get medical help or contact a Poison Control Center (1-800-222-1222) right away.

Directions

- before using this product read the enclosed consumer information leaflet for complete directions and information
- adults and children 12 years of age and over:
  - applicator:insert 1 applicatorful into the vagina at bedtime for 7 nights in a row. Wash applicator after use.
  - use the same tube of cream if you have itching and irritation on the skin outside the vagina. Squeeze a small amount of cream onto your fingertip. Apply to itchy, irritated skin outside the vagina (vulva). Use 2 times daily for up to 7 days as needed.
- children under 12 years of age: ask a doctor

Other information

- to open tube: unscrew cap, lift tab, and pull to remove foil seal prior to use
- do not use if foil seal on tube opening is broken or missing
- do not purchase if carton is open
- store at room temperature 20°to 25°C (68°to 77°F)
- before using any medication, read all label direction. Keep carton, it contains important information.
- Relabeled By: Preferred Pharmaceuticals Inc.

Inactive ingredients

benzoic acid, butylated hydroxyanisole, mineral oil, oleoyl polyoxylglycerides, pegoxol 7 stearate, purified water

Questions?

Call 1-877-753-3935 Monday-Friday 9AM-5PM EST

Principal display panel

Compare to the active ingredient in Monistat® 7 Vaginal Cream*

Miconazole 7

Miconazole Nitrate Vaginal Cream, USP 2%

(Miconazole Nitrate 100 mg per applicator)

2%

Vaginal Antifungal

Cures most vaginal yeast infections

Relieves associated external itching and irritation

7 day vaginal cream (1 tube) with 1 reusable applicator

NET WT OZ (g) Tube

*This product is not affiliated with, manufactured by, or produced by the makers or owners of Monistat®.

Distributed by:

MAJOR® PHARMACEUTICALS

Indianapolis, IN 46268

www.majorpharmaceuticals.com